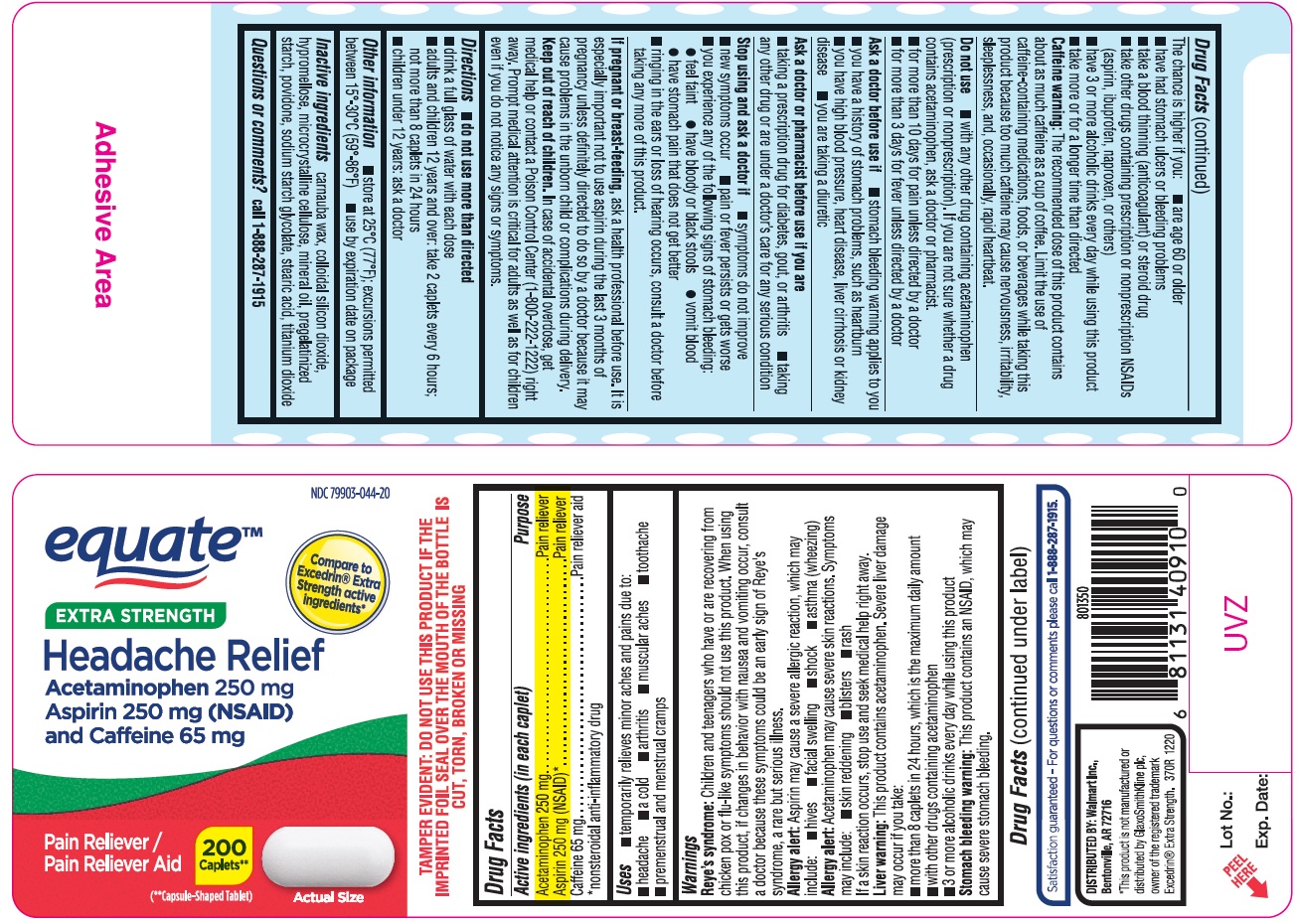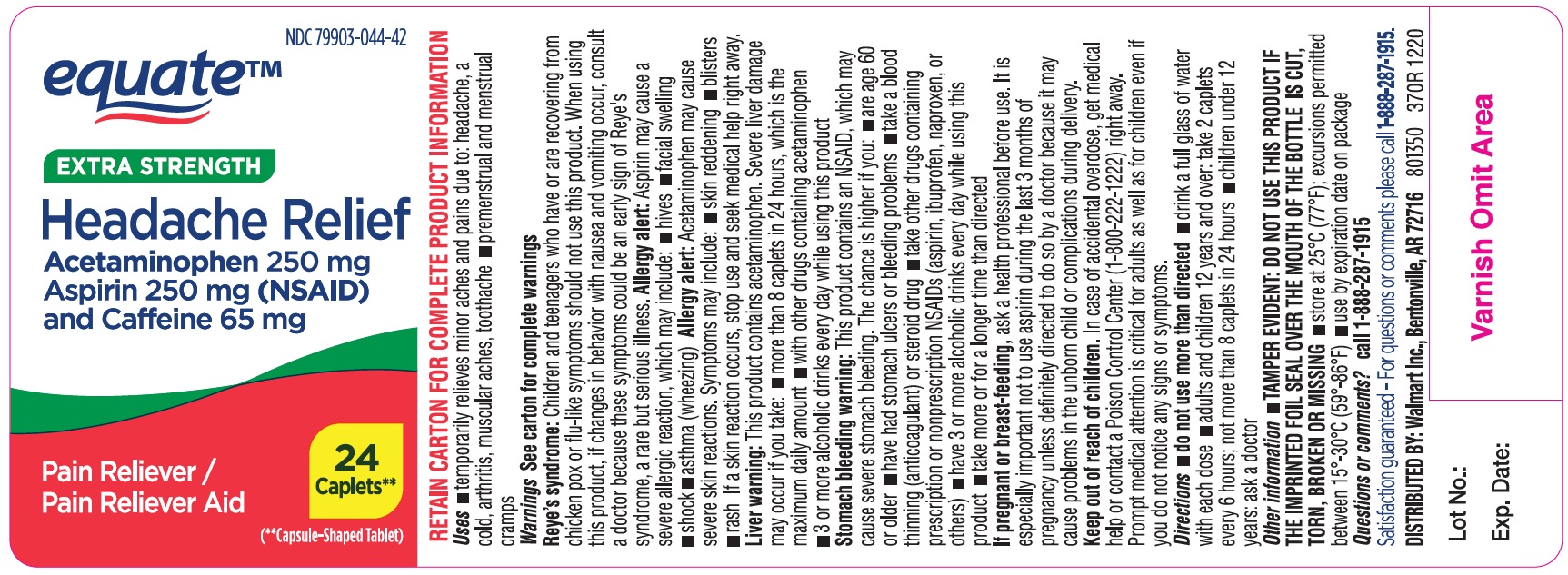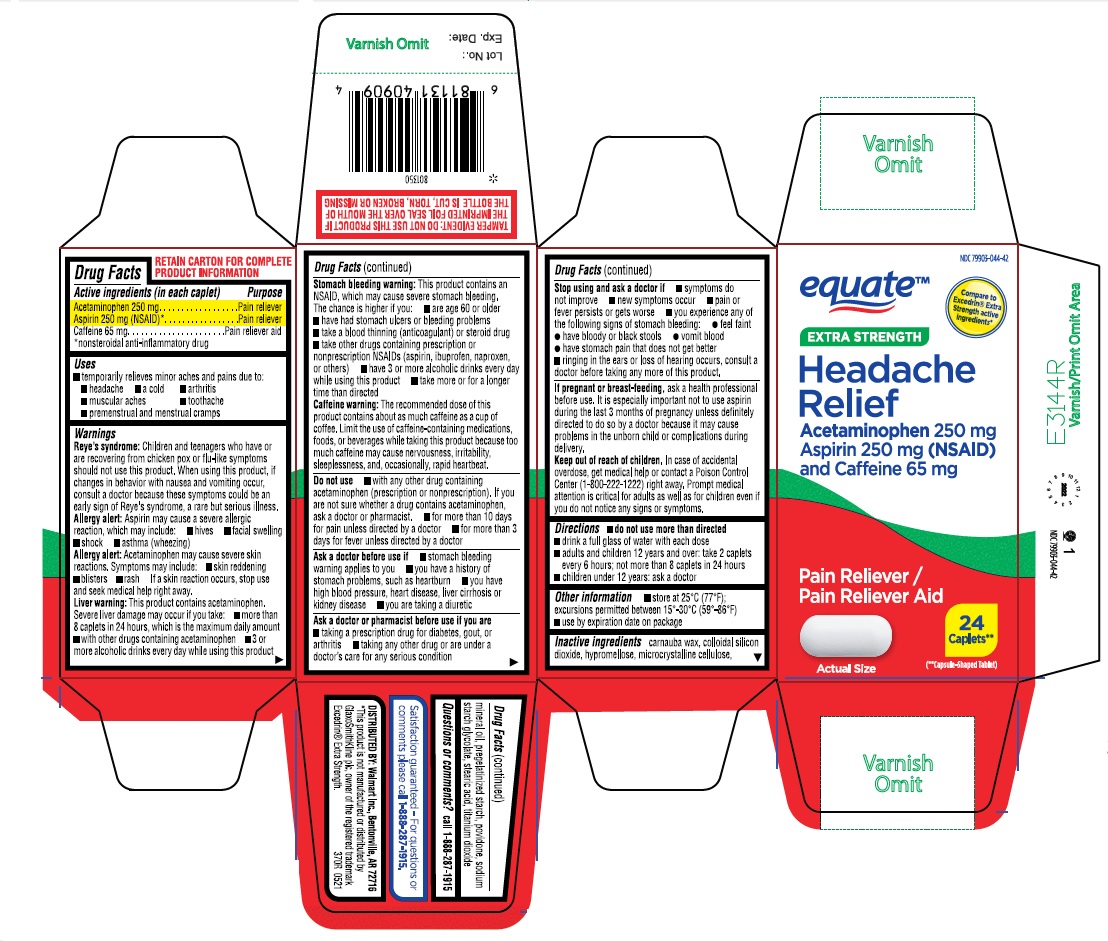 DRUG LABEL: EXTRA STRENGTH HEADACHE RELIEF
NDC: 79903-044 | Form: TABLET, COATED
Manufacturer: WAL-MART STORES INC
Category: otc | Type: HUMAN OTC DRUG LABEL
Date: 20250716

ACTIVE INGREDIENTS: ASPIRIN 250 mg/1 1; ACETAMINOPHEN 250 mg/1 1; CAFFEINE 65 mg/1 1
INACTIVE INGREDIENTS: SILICON DIOXIDE; CELLULOSE, MICROCRYSTALLINE; POVIDONE; STEARIC ACID; CARNAUBA WAX; SODIUM STARCH GLYCOLATE TYPE A CORN; TITANIUM DIOXIDE; HYPROMELLOSES; MINERAL OIL; STARCH, CORN

370R Walmart 79903-044 Acetaminophen 250mg, Aspirin 250 mg & Caffeine 65 mg 24 ct and 200 ct

Active ingredients (in each caplet)
Acetaminophen 250 mg
Aspirin 250 mg (NSAID)*
Caffeine 65 mg
*nonsteroidal anti-inflammatory drug

Purpose
Pain reliever
Pain reliever
Pain reliever aid

Uses
temporarily relieves minor aches and pains due to:
• headache
• a cold
• arthritis
• muscular aches
• toothache
• premenstrual and menstrual cramps

Warnings

Reye’s syndrome: Children and teenagers who have or are recovering from chicken pox or flu-like symptoms should not use this product. When using this product, if changes in behavior with nausea and vomiting occur, consult a doctor because these symptoms could be an early sign of Reye’s syndrome, a rare but serious illness.
Allergy alert: Aspirin may cause a severe allergic reaction, which may include:

• hives
• facial swelling
• shock

• asthma (wheezing)

Allergy alert: Acetaminophen may cause severe skin reactions. Symptoms may include:
• skin reddening
• blisters
• rash
If a skin reaction occurs, stop use and seek medical help right away.
Liver warning: This product contains acetaminophen. Severe liver damage may occur if you take:
• more than 8 caplets in 24 hours, which is the maximum daily amount
• with other drugs containing acetaminophen
• 3 or more alcoholic drinks every day while using this product

Stomach bleeding warning: This product contains an NSAID, which may cause severe stomach bleeding. The chance is higher if you:
• are age 60 or older
• have had stomach ulcers or bleeding problems
• take a blood thinning (anticoagulant) or steroid drug
• take other drugs containing prescription or nonprescription NSAIDs (aspirin, ibuprofen, naproxen, or others)
• have 3 or more alcoholic drinks every day while using this product
• take more or for a longer time than directed
Caffeine warning: The recommended dose of this product contains about as much caffeine as a cup of coffee. Limit the use of caffeine-containing medications, foods, or beverages while taking this product because too much caffeine may cause nervousness, irritability, sleeplessness, and, occasionally, rapid heartbeat.

Do not use

- with any other drug containing acetaminophen (prescription or nonprescription). If you are not sure whether a drug contains acetaminophen, ask a doctor or pharmacist.
- for more than 10 days for pain unless directed by a doctor
- for more than 3 days for fever unless directed by a doctor

Ask a doctor before use if
• stomach bleeding warning applies to you

• you have a history of stomach problems, such as heartburn

• you have high blood pressure, heart disease, liver cirrhosis, or kidney disease

• you are taking a diuretic

Ask a doctor or pharmacist before use if you are
• taking a prescription drug for diabetes, gout, or arthritis
• taking any other drug or are under a doctor’s care for any serious condition

Stop use and ask a doctor if

- symptoms do not improve
- new symptoms occur
- pain or fever persists or gets worse
- you experience any of the following signs of stomach bleeding:

feel faint

have bloody or black stools

vomit blood

have stomach pain that does not get better

- ringing in the ears or loss of hearing occurs, consult a doctor before taking any more of this product

PREGNANCY OR BREAST FEEDING

If pregnant or breast-feeding, ask a health professional before use. It is especially important not to use aspirin during the last 3 months of pregnancy unless definitely directed to do so by a doctor because it may cause problems in the unborn child or complications during delivery.

Keep out of reach of children
In case of accidental overdose, get medical help or contact a Poison Control Center (1-800-222-1222) right away. Prompt medical attention is critical for adults as well as for children even if you do not notice any signs or symptoms.

Directions

• do not use more than directed
• drink a full glass of water with each dose
• adults and children 12 years and over: take 2 caplets every 6 hours; not more than 8 caplets in 24 hours
• children under 12 years: ask a doctor

Other information

• store at 20°- 25°C (68°- 77°F) excursions permitted between 15°-30°C (59°-86°F)
• use by expiration date on package

INACTIVE INGREDIENT

Inactive ingredients carnauba wax, colloidal silicon dioxide, hypromellose, microcrystalline cellulose, mineral oil, pregelatinized starch, povidone, sodium starch glycolate, stearic acid, titanium dioxide

Questions or comments?

Call 1-877-290-4008